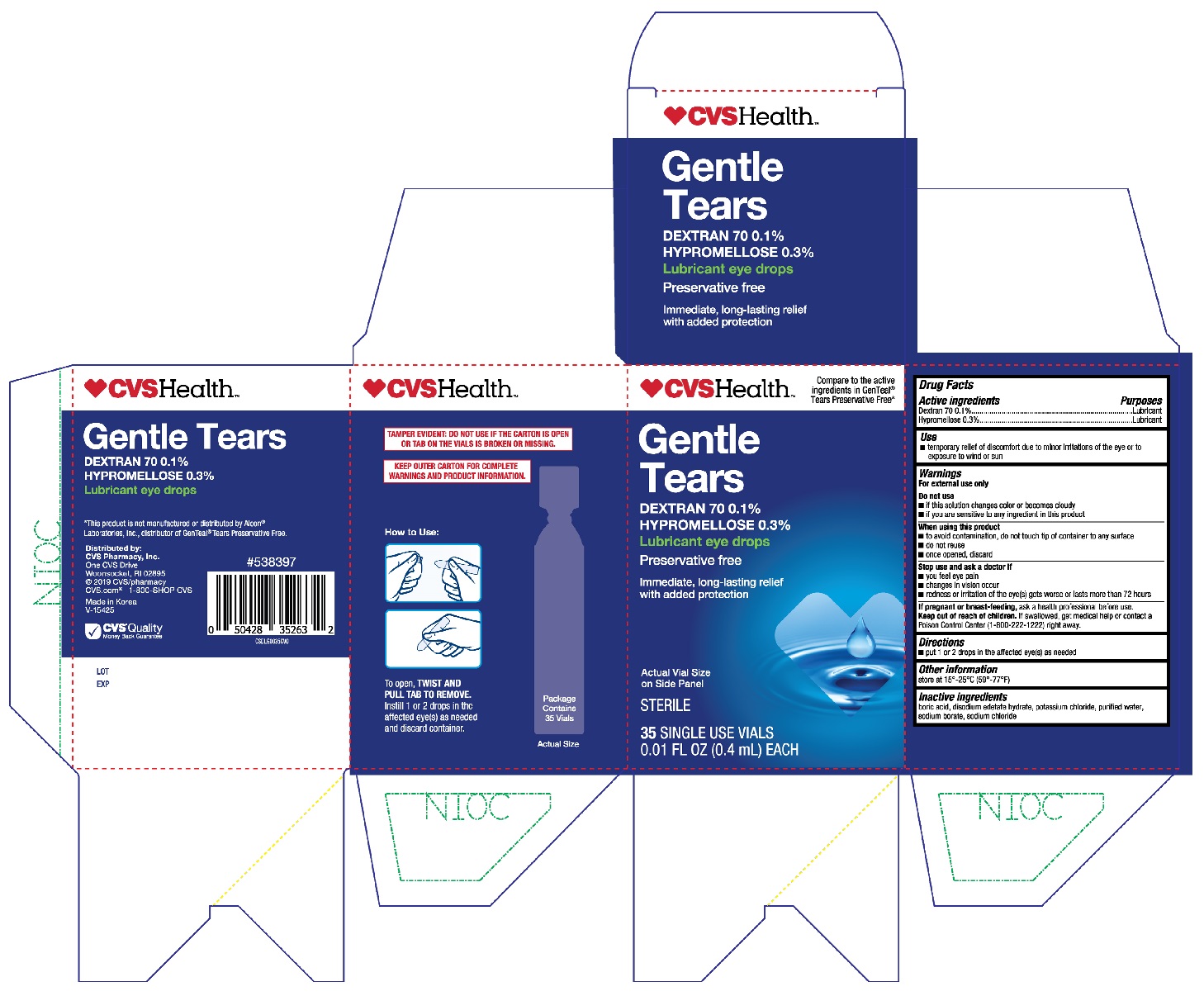 DRUG LABEL: CVS Gentle Tears
NDC: 69842-474 | Form: SOLUTION/ DROPS
Manufacturer: CVS Pharmacy, Inc.
Category: otc | Type: HUMAN OTC DRUG LABEL
Date: 20251230

ACTIVE INGREDIENTS: HYPROMELLOSE, UNSPECIFIED 0.3 g/100 mL; DEXTRAN 70 0.1 g/100 mL
INACTIVE INGREDIENTS: EDETATE DISODIUM; SODIUM BORATE; SODIUM CHLORIDE; BORIC ACID; POTASSIUM CHLORIDE; WATER

CVS Gentle Tears (PLD)

Active ingredients

Dextran 70 0.1%

Hypromellose 0.3%

Purposes

Lubricant

Lubricant

Use

- temporary relief of discomfort due to minor irritations of the eye or to exposure to wind or sun

Warnings

For external use only

Do not use

- if this solution changes color or becomes cloudy
- if you are sensitive to any ingredient in this product

When using this product

- to avoid contamination, do not touch tip of container to any surface
- do not reuse
- once opened, discard

Stop use and ask a doctor if

- you feel eye pain
- changes in vision occur
- redness or irritation of the eye(s) gets worse or lasts more than 72 hours

If pregnant or breast-feeding,

ask a health professional before use.

Keep out of reach of children.

If swallowed, get medical help or contact a Poison Control Center (1-800-222-1222) right away.

Directions

- put 1 or 2 drops in the affected eye(s) as needed

Other information

store at 15°-25°C (59°-77°F)

Inactive ingredients

boric acid, disodium edetate hydrate, potassium chloride, purified water, sodium borate, sodium chloride